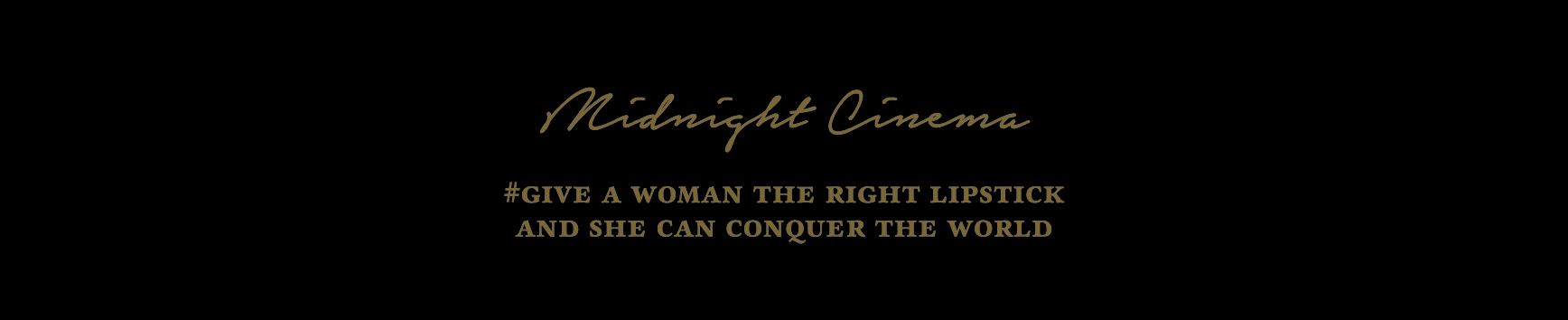 DRUG LABEL: MIDNIGHT CINEMA LA BELLE IN ROUGE 01. DANCING IN MONACO
NDC: 70905-0016 | Form: LIPSTICK
Manufacturer: Dr. Althea
Category: otc | Type: HUMAN OTC DRUG LABEL
Date: 20170414

ACTIVE INGREDIENTS: DIMETHICONE 7.4 g/100 g
INACTIVE INGREDIENTS: TITANIUM DIOXIDE; .ALPHA.-TOCOPHEROL ACETATE

Drug Facts

ACTIVE INGREDIENT

DIMETHICONE

INACTIVE INGREDIENT

ISONONYL ISONONANOATE, PHENYL TRIMETHICONE, SILICA, JOJOBA ESTERS, TOCOPHERYL ACETATE, TITANIUM DIOXIDE, ETC.

PURPOSE

LIP COLOR

keep out of reach of the children

INDICATIONS AND USAGE

Take suitable amount of product and put on the lip.

WARNINGS

Caution：

1. If the following symptoms occur after using the product , stop using the product immediately and consult with a dermatologist

(1) Occurrence of red spots, swelling, itchiness, and other skin stimulation.

(2) If the symptoms above occur after the application area being exposed to direct sunlight

2. Do not use on wounds.

3. Precaution for Storage and Handling

(1) Keep out of reach of infants and children

(2) Do not store in a place exposed to direct sunlight.

DOSAGE AND ADMINISTRATION

for external use only